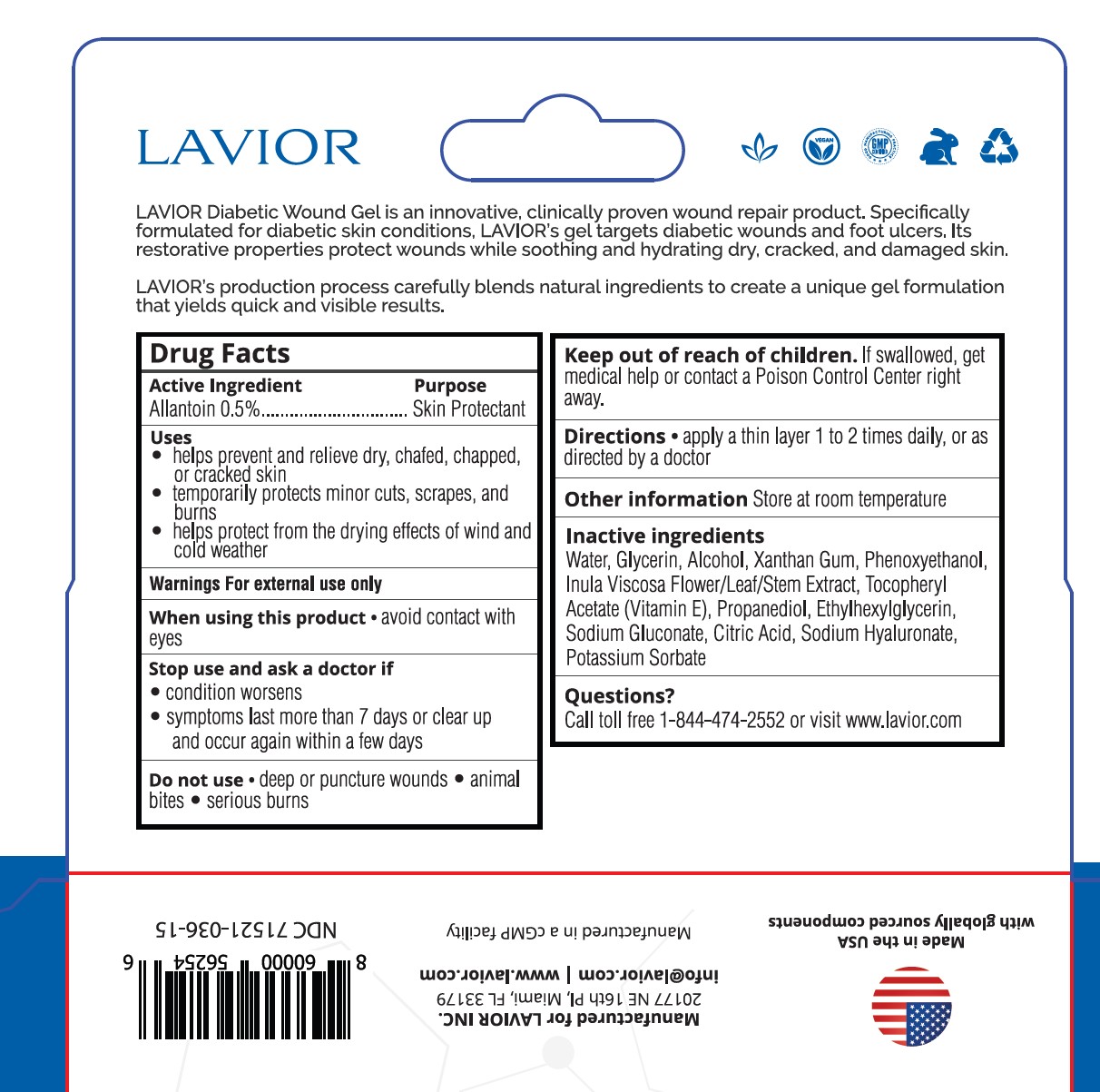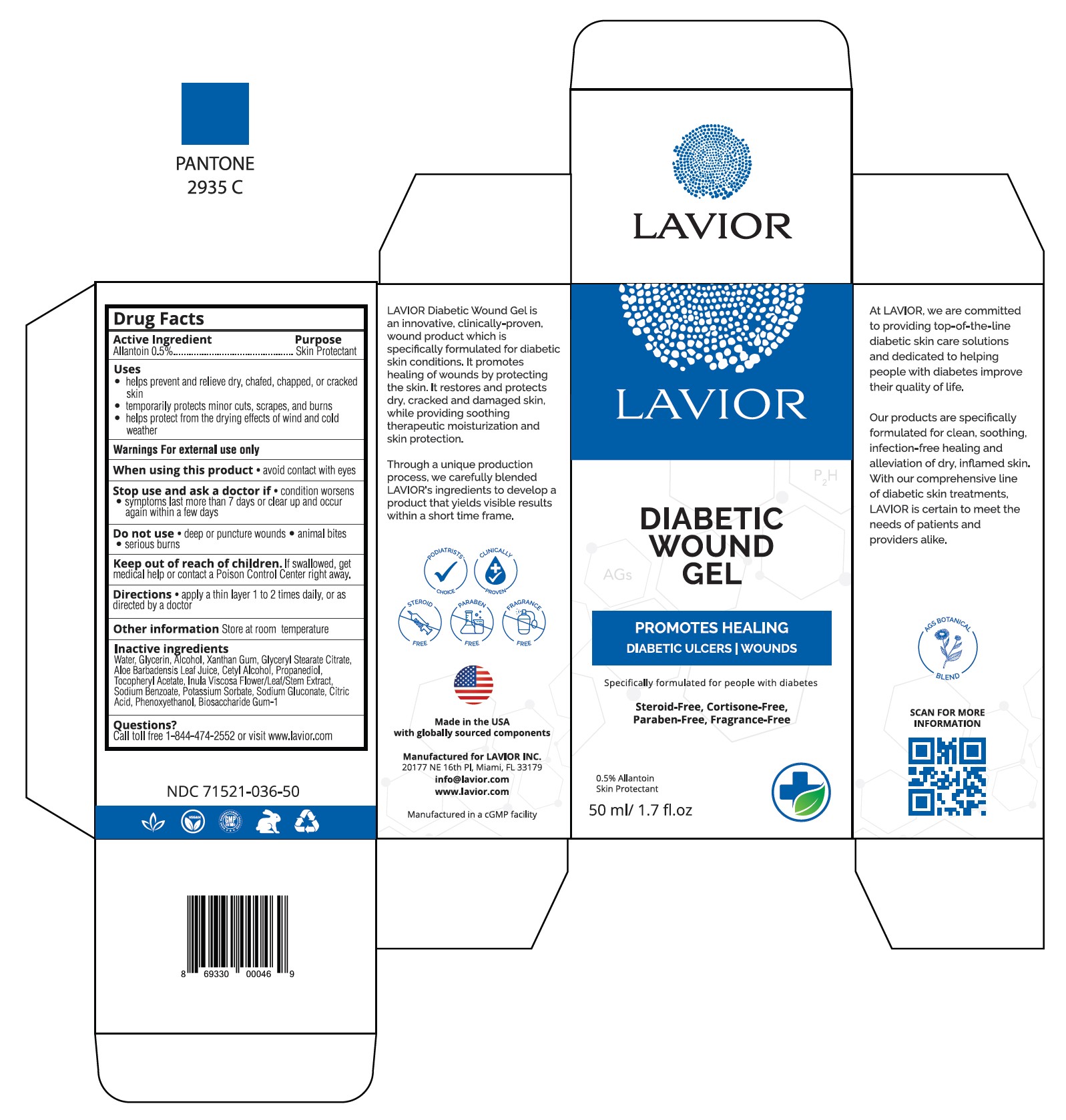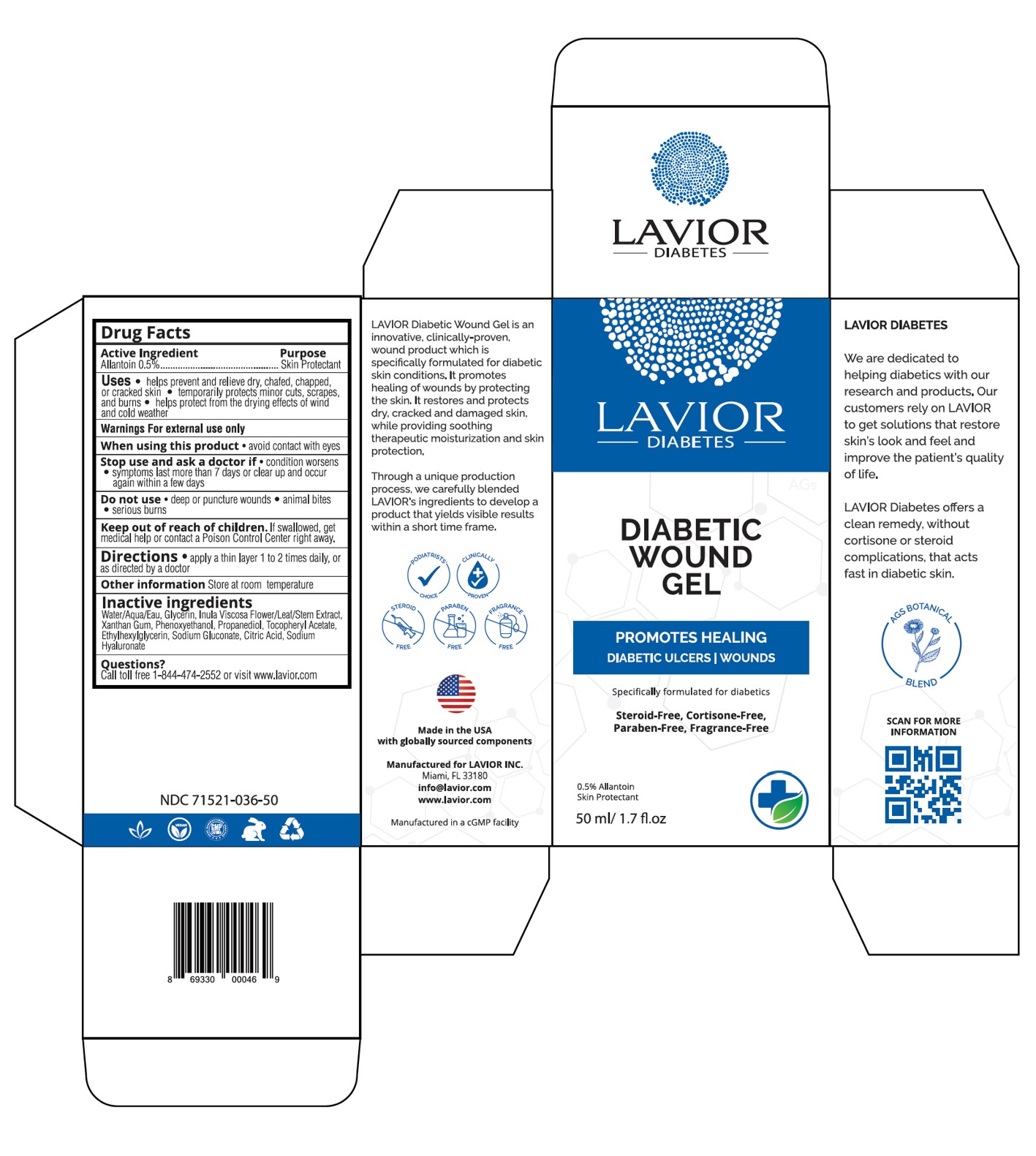 DRUG LABEL: Diabetic Wound Gel
NDC: 71521-036 | Form: GEL
Manufacturer: Lavior Pharma Inc
Category: otc | Type: HUMAN OTC DRUG LABEL
Date: 20241022

ACTIVE INGREDIENTS: ALLANTOIN 1 g/100 g
INACTIVE INGREDIENTS: PHENOXYETHANOL; .ALPHA.-TOCOPHEROL ACETATE; HYALURONATE SODIUM; XANTHAN GUM; PROPANEDIOL; ETHYLHEXYLGLYCERIN; CITRIC ACID MONOHYDRATE; SODIUM GLUCONATE; DITTRICHIA VISCOSA WHOLE

Active Ingredients

Allantoin 0.5%.......................Skin Protectant

Purpose

Skin Protectant

Uses

- helps prevent and relieve dry, chafed, chapped, or cracked skin
- temporarily protects minor cuts, scrapes, and burns
- helps protect from the drying effects of wind and cold weather

Warnings

For external use only

When using this product

- avoid contact with eyes

Stop use and ask a doctor if

- condition worsens
- symptoms last more than 7 days, clear up and occur again within a few days

Do not use

- deep or puncture wounds
- animal bites
- serious burns

Keep out of reach of children

If swallowed, get medical help or contact a Poison Control Center right away.

Directions

apply a thin layer 1 to 2 times daily, or as directed by a doctor

Other information

store at room temperature